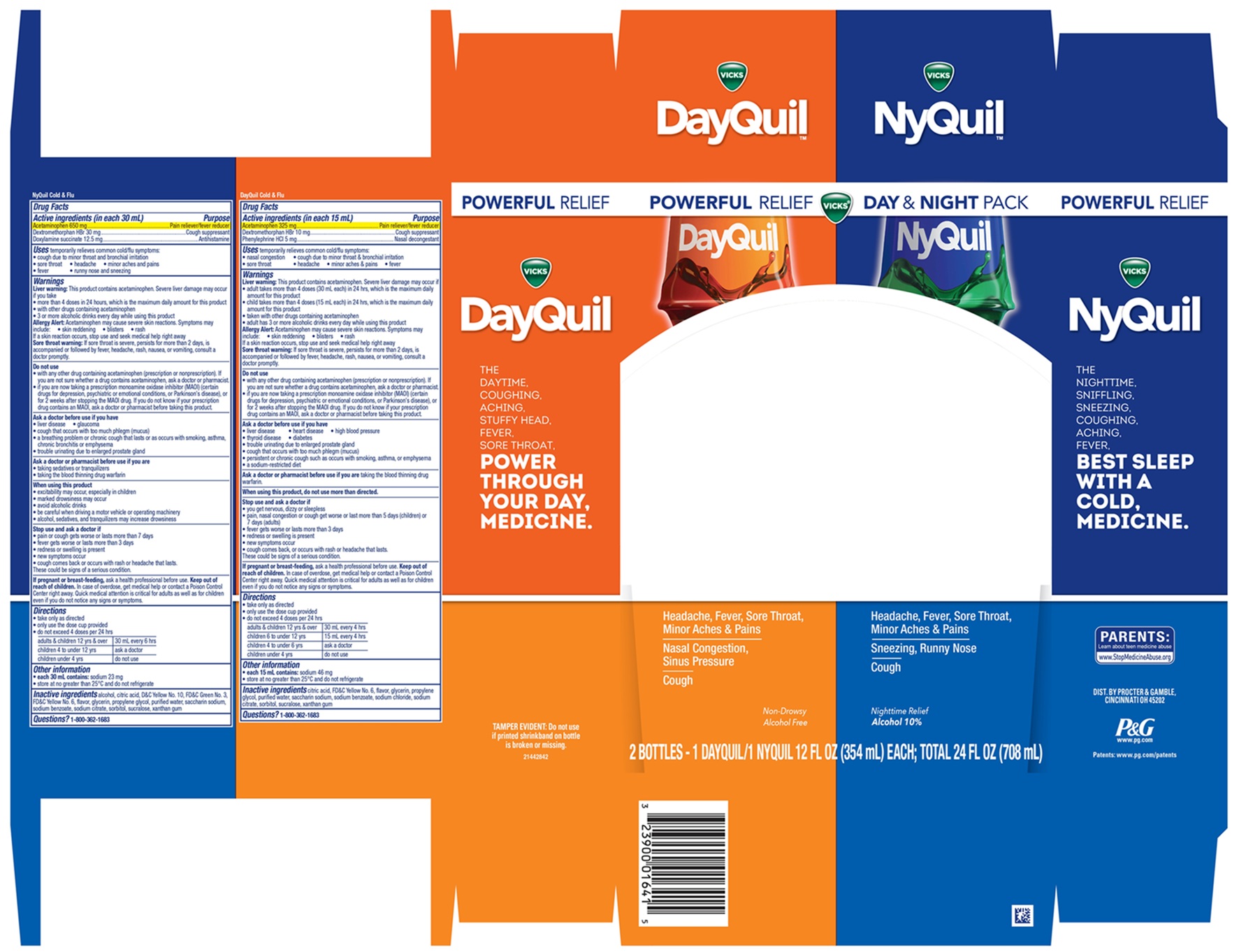 DRUG LABEL: Vicks DayQuil and Vicks NyQuil
NDC: 37000-033 | Form: KIT | Route: ORAL
Manufacturer: The Procter & Gamble Manufacturing Company
Category: otc | Type: HUMAN OTC DRUG LABEL
Date: 20260220

ACTIVE INGREDIENTS: ACETAMINOPHEN 325 mg/15 mL; DEXTROMETHORPHAN HYDROBROMIDE 10 mg/15 mL; PHENYLEPHRINE HYDROCHLORIDE 5 mg/15 mL; DOXYLAMINE SUCCINATE 12.5 mg/30 mL; ACETAMINOPHEN 650 mg/30 mL; DEXTROMETHORPHAN HYDROBROMIDE 30 mg/30 mL
INACTIVE INGREDIENTS: CITRIC ACID MONOHYDRATE; FD&C YELLOW NO. 6; GLYCERIN; PROPYLENE GLYCOL; WATER; SACCHARIN SODIUM; SODIUM BENZOATE; SODIUM CHLORIDE; SODIUM CITRATE; SORBITOL; SUCRALOSE; XANTHAN GUM; ALCOHOL; CITRIC ACID MONOHYDRATE; FD&C GREEN NO. 3; D&C YELLOW NO. 10; PROPYLENE GLYCOL; WATER; SACCHARIN SODIUM; SODIUM BENZOATE; SODIUM CITRATE; XANTHAN GUM; FD&C YELLOW NO. 6

Vicks®DayQuil™ and Vicks®NyQuil™
Cold & Flu Convenience Pack

NyQuil Cold & Flu

Drug Facts

Active ingredients (in each 30 mL)

Acetaminophen 650 mg
Dextromethorphan HBr 30 mg
Doxylamine succinate 12.5 mg

Purpose

Pain reliever/ fever reducer
Cough suppressant
Antihistamine

Uses

temporarily relieves common cold/flu symptoms:

- cough due to minor throat & bronchial irritation
- sore throat
- headache
- minor aches & pains
- fever
- runny nose and sneezing

Warnings

Liver warning:

This product contains acetaminophen. Severe liver damage may occur if you take

- more than 4 doses in 24 hours, which is the maximum daily amount for this product
- with other drugs containing acetaminophen
- 3 or more alcoholic drinks every day while using this product

Allergy Alert:

Acetaminophen may cause severe skin reactions. Symptoms may include:

- Skin reddening
- Blisters
- Rash

If a skin reaction occurs, stop use and seek medical help right away

Sore throat warning:

If sore throat is severe, persists for more than 2 days, is accompanied or followed by fever, headache, rash, nausea, or vomiting, consult a doctor promptly.

Do not use

- with any other drug containing acetaminophen (prescription or nonprescription). If you are not sure whether a drug contains acetaminophen, ask a doctor or pharmacist.
- if you are now taking a prescription monoamine oxidase inhibitor (MAOI) (certain drugs for depression, psychiatric or emotional conditions, or Parkinson's disease), or for 2 weeks after stopping the MAOI drug. If you do not know if your prescription drug contains an MAOI, ask a doctor or pharmacist before taking this product.

Ask a doctor before use if you have

- liver disease
- glaucoma
- cough that occurs with too much phlegm (mucus)
- a breathing problem or chronic cough that lasts or as occurs with smoking, asthma, chronic bronchitis, or emphysema
- trouble urinating due to enlarged prostate gland

Ask a doctor or pharmacist before use if you are

- taking sedatives or tranquilizers
- taking the blood thinning drug warfarin

When using this product

- excitability may occur, especially in children
- marked drowsiness may occur
- avoid alcoholic drinks
- be careful when driving a motor vehicle or operating machinery
- alcohol, sedatives, and tranquilizers may increase drowsiness

Stop use and ask a doctor if

- pain or cough gets worse or lasts more than 7 days
- fever gets worse or lasts more than 3 days
- redness or swelling is present
- new symptoms occur
- cough comes back or occurs with rash or headache that lasts

These could be signs of a serious condition.

PREGNANCY OR BREAST FEEDING

If pregnant or breast-feeding,ask a health professional before use.

Keep out of reach of children.

In case of overdose, get medical help or contact a Poison Control Center right away. Quick medical attention is critical for adults as well as for children even if you do not notice any signs or symptoms.

Directions

- take only as directed
- only use the dose cup provided
- do not exceed 4 doses per 24 hrs

adults & children 12 yrs & over | 30 mL every 6 hrs
children 4 to under 12 yrs | ask a doctor
children under 4 yrs | do not use

Other information

- each 30 mL contains: sodium 23 mg
- store at no greater than 25°C and do not refrigerateand do not refrigerate

Inactive ingredients

alcohol, citric acid, D&C Yellow No. 10, FD&C Green No. 3, FD&C Yellow No. 6, flavor, glycerin, propylene glycol, purified water, saccharin sodium,, sodium benzoate, sodium citrate, sorbitol, sucralose, xanthan gum

Questions?

1-800-362-1683

Dist. by Procter & Gamble, Cincinnati OH 45202

DayQuil Cold & Flu

Drug Facts

Active ingredients (in each 15 mL)

Acetaminophen 325 mg
Dextromethorphan HBr 10 mg
Phenylephrine HCI 5 mg

Purpose

Pain reliever/Fever reducer
Cough suppressant
Nasal decongestant

Uses

temporarily relieves common cold/flu symptoms:

- nasal congestion
- cough due to minor throat & bronchial irritation
- sore throat
- headache
- minor aches & pains
- fever

Warnings

Liver warning:

This product contains acetaminophen. Severe liver damage may occur if

- adults take more than 4 doses (30 mL each) in 24 hours, which is the maximum daily amount for this product
- child take more than 4 doses (15 mL each) in 24 hours, which is the maximum daily amount for this product
- with other drugs containing acetaminophen
- adult has 3 or more alcoholic drinks every day while using this product

Allergy Alert:

Acetaminophen may cause severe skin reactions. Symptoms may include:

- Skin reddening
- Blisters
- Rash

If a skin reaction occurs, stop use and seek medical help right away

Sore throat warning:

If sore throat is severe, persists for more than 2 days, is accompanied or followed by fever, headache, rash, nausea, or vomiting, consult a doctor promptly.

Do not use

- with any other drug containing acetaminophen (prescription or nonprescription). If you are not sure whether a drug contains acetaminophen, ask a doctor or pharmacist.
- if you are now taking a prescription monoamine oxidase inhibitor (MAOI) (certain drugs for depression, psychiatric or emotional conditions, or Parkinson's disease), or for 2 weeks after stopping the MAOI drug. If you do not know if your prescription drug contains an MAOI, ask a doctor or pharmacist before taking this product.

Ask a doctor before use if you have

- liver disease
- heart disease
- high blood pressure
- thyroid disease
- diabetes
- trouble urinating due to enlarged prostate gland
- cough that occurs with too much phlegm (mucus)
- persistent or chronic cough such as occurs with smoking, asthma, or emphysema
- a sodium-restricted diet

Ask a doctor or pharmacist before use if you are

taking the blood thinning drug warfarin.

When using this product,

do not use more than directed.

Stop use and ask a doctor if

- you get nervous, dizzy or sleepless
- pain, nasal congestion or cough get worse or last more than 5 days (children) or 7 days (adults)
- fever gets worse or lasts more than 3 days
- redness or swelling is present
- new symptoms occur
- cough comes back, or occurs with rash or headache that lasts.

These could be signs of a serious condition.

PREGNANCY OR BREAST FEEDING

If pregnant or breast-feeding,ask a health professional before use.

Keep out of reach of children.

In case of overdose, get medical help or contact a Poison Control Center right away. Quick medical attention is critical for adults as well as for children even if you do not notice any signs or symptoms.

Directions

- take only as directed
- only use the dose cup provided
- do not exceed 4 doses per 24 hrs

adults & children 12 yrs & over | 30 mL every 4 hrs
children 6 to under 12 yrs | 15 mL every 4 hrs
children 4 to under 6 yrs | ask a doctor
children under 4 yrs | do not use

Other information

- each 15 mL contains: sodium 46 mg
- store at no greater than 25°C and do not refrigerate.

Inactive ingredients

citric acid, FD&C Yellow No. 6, flavor, glycerin, propylene glycol, purified water, saccharin sodium, sodium benzoate,
sodium chloride, sodium citrate, sorbitol, sucralose, xanthan gum

Questions?

1-800-362-1683

TAMPER EVIDENT:Do not use if printer shrinkband on bottle is broken or missing.

PRINCIPAL DISPLAY PANEL - Convenience Pack

POWERFUL

RELIEF

Day & Night Pack

VICKS®

DayQuil™

COLD & FLU

Acetaminophen,Phenylephrine HCl, Dextromethorphan HBr,

Headache, Fever, Sore Throat, Minor Aches & Pains

Nasal Congestion, Sinus Pressure

Cough

NyQuil™

COLD & FLU

Acetaminophen, Doxylamine Succinate, Dextromethorphan HBr

Headache, Fever, Sore Throat, Minor Aches & Pains

Sneezing, Runny Nose

Cough

Nighttime Relief

Alcohol 10%

2 BOTTLES – 1 DAYQUIL/1 NYQUIL 12 FL OZ (354 mL) EACH; TOTAL 24 FL OZ (708 mL)